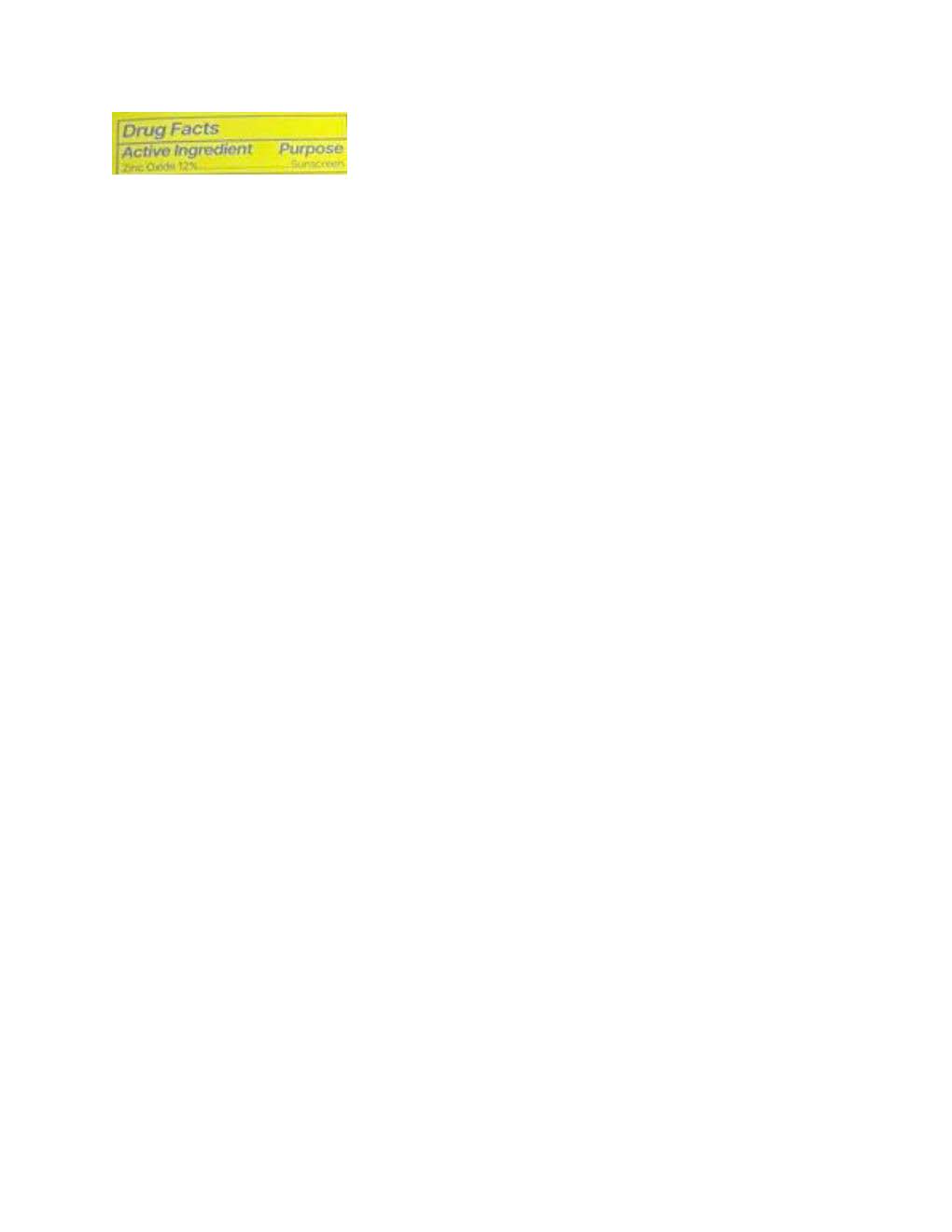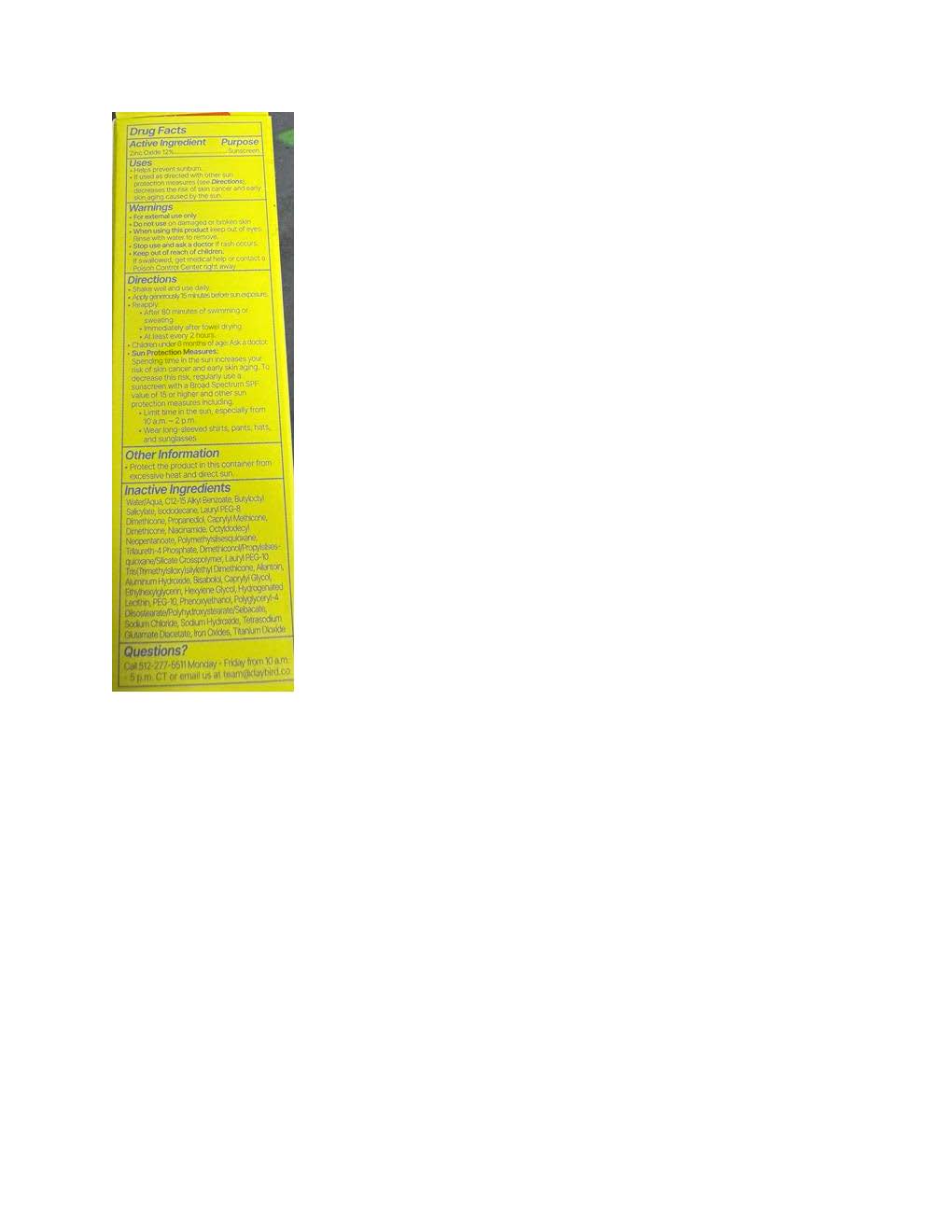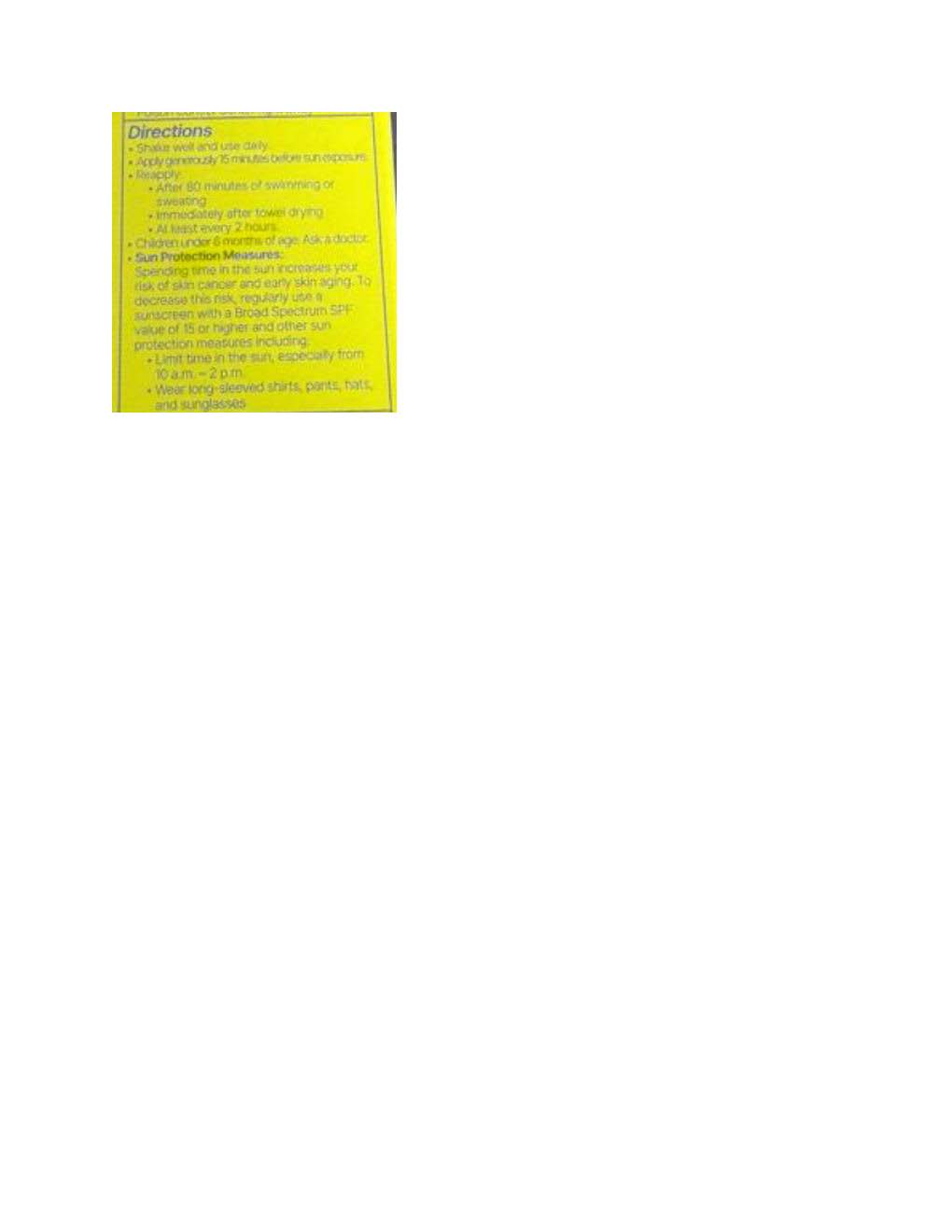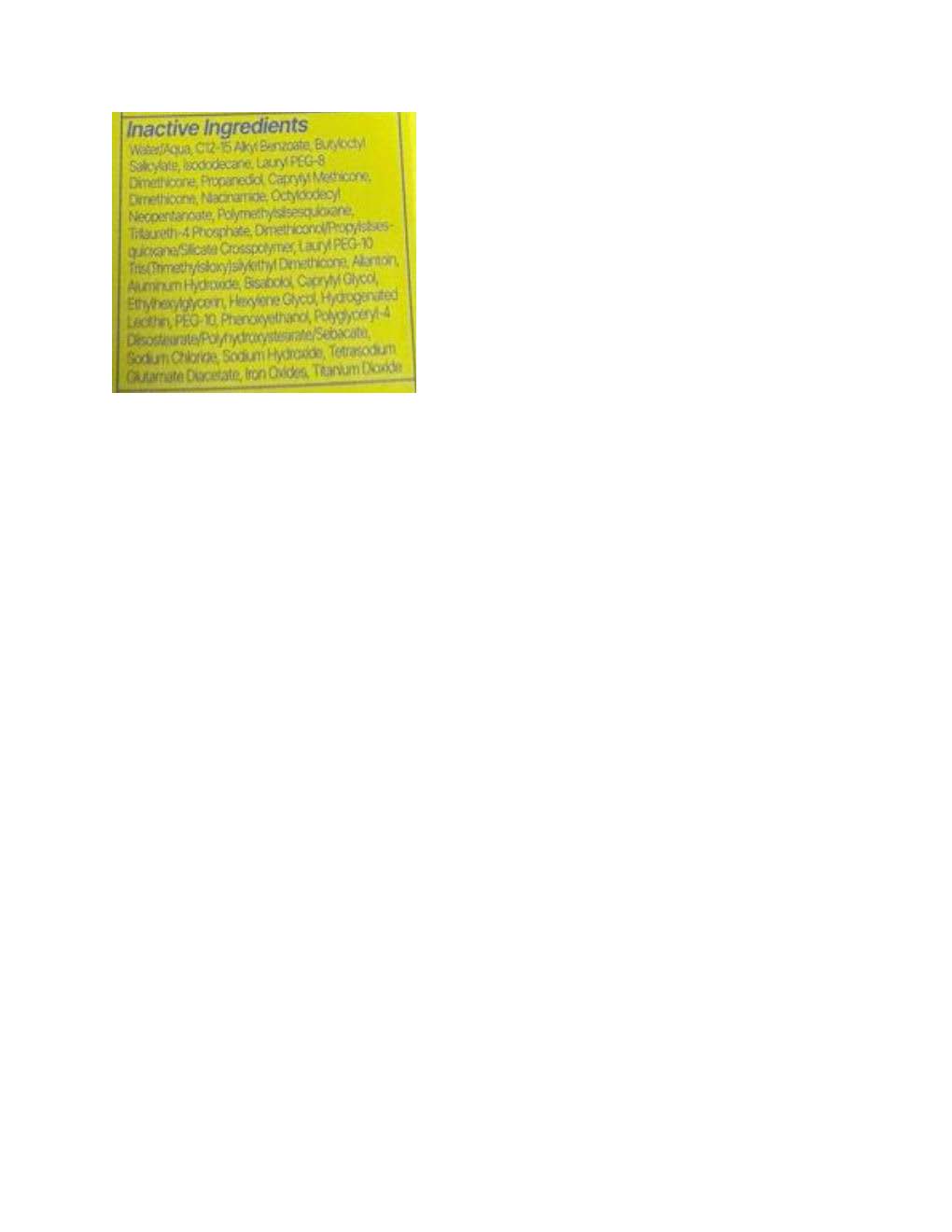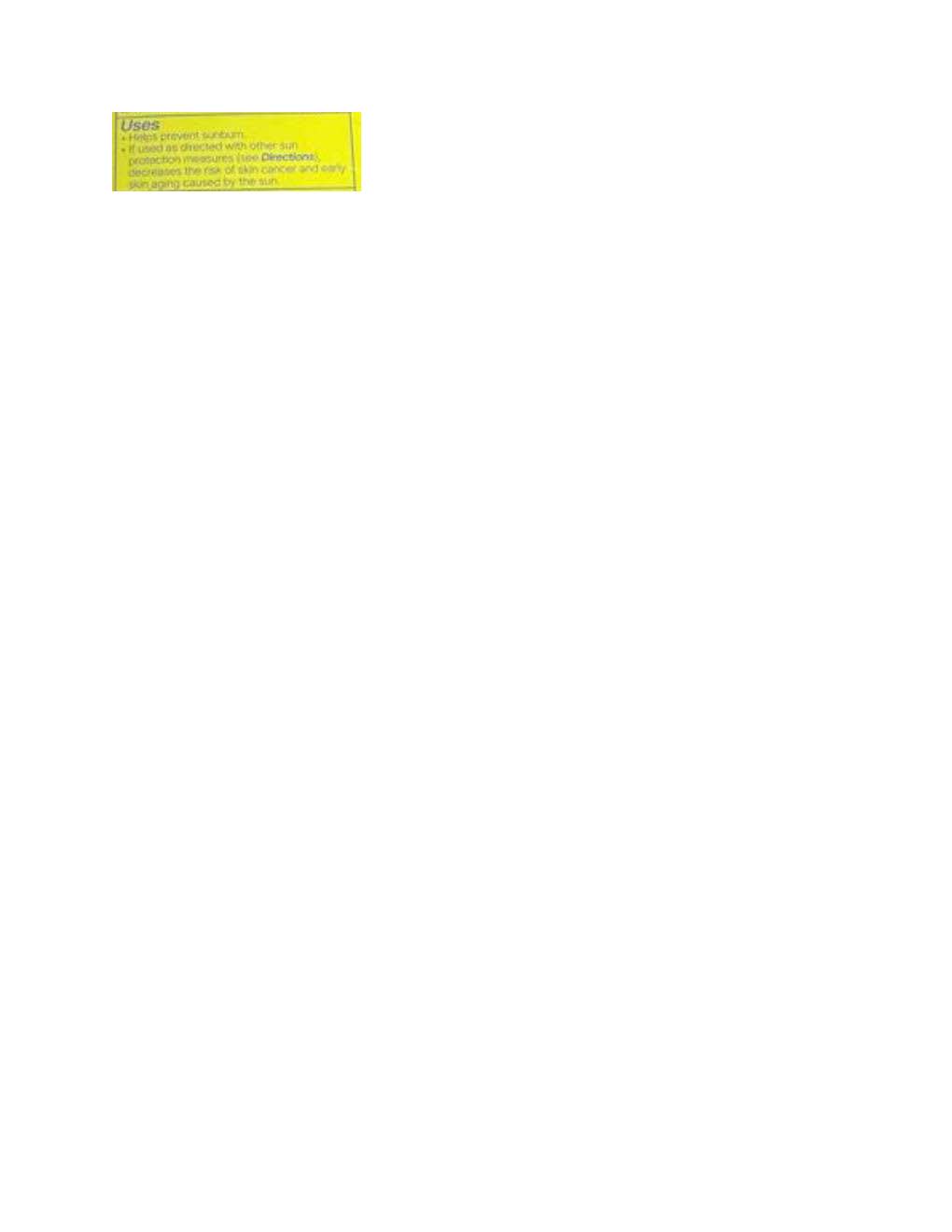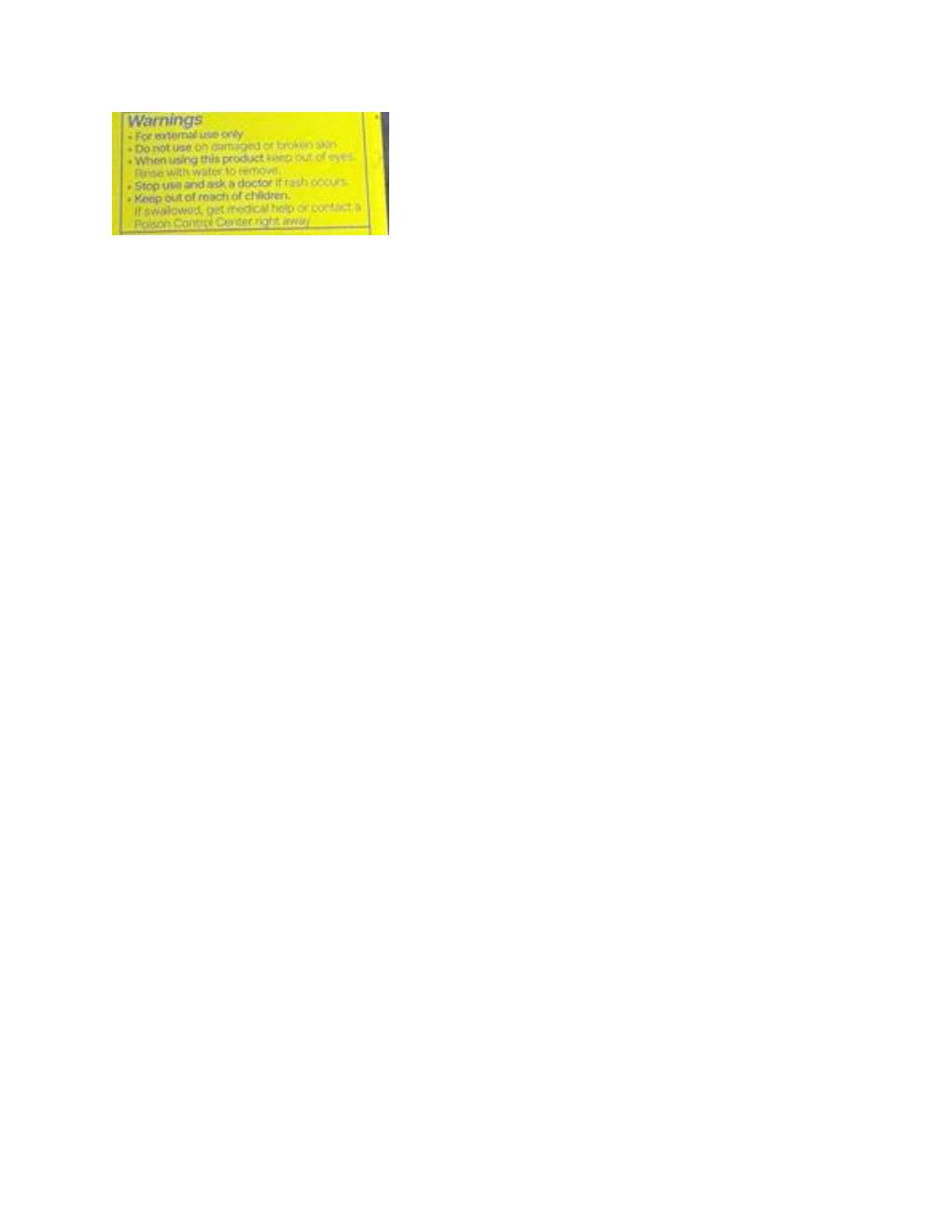 DRUG LABEL: Daybird 4-in-1 Skin Tint Serum
NDC: 82417-1210 | Form: LOTION
Manufacturer: Resette, Inc.
Category: otc | Type: HUMAN OTC DRUG LABEL
Date: 20251009

ACTIVE INGREDIENTS: ZINC OXIDE 132 mg/1 mL
INACTIVE INGREDIENTS: FERRIC OXIDE YELLOW; LAURYL PEG-8 DIMETHICONE (300 CPS); ALKYL (C12-15) BENZOATE; POLYMETHYLSILSESQUIOXANE (4.5 MICRONS); DIMETHICONE; WATER; NIACINAMIDE; ETHYLHEXYLGLYCERIN; HEXYLENE GLYCOL; TRILAURETH-4 PHOSPHATE; DIMETHICONOL/PROPYLSILSESQUIOXANE/SILICATE CROSSPOLYMER (450000000 MW); PROPANEDIOL; TETRASODIUM GLUTAMATE DIACETATE; FERRIC OXIDE RED; SODIUM CHLORIDE; PHENOXYETHANOL; BUTYLOCTYL SALICYLATE; OCTYLDODECYL NEOPENTANOATE; ISODODECANE; .ALPHA.-BISABOLOL, (+)-; ALLANTOIN

Daybird 4-in-1 Skin Tint Serum